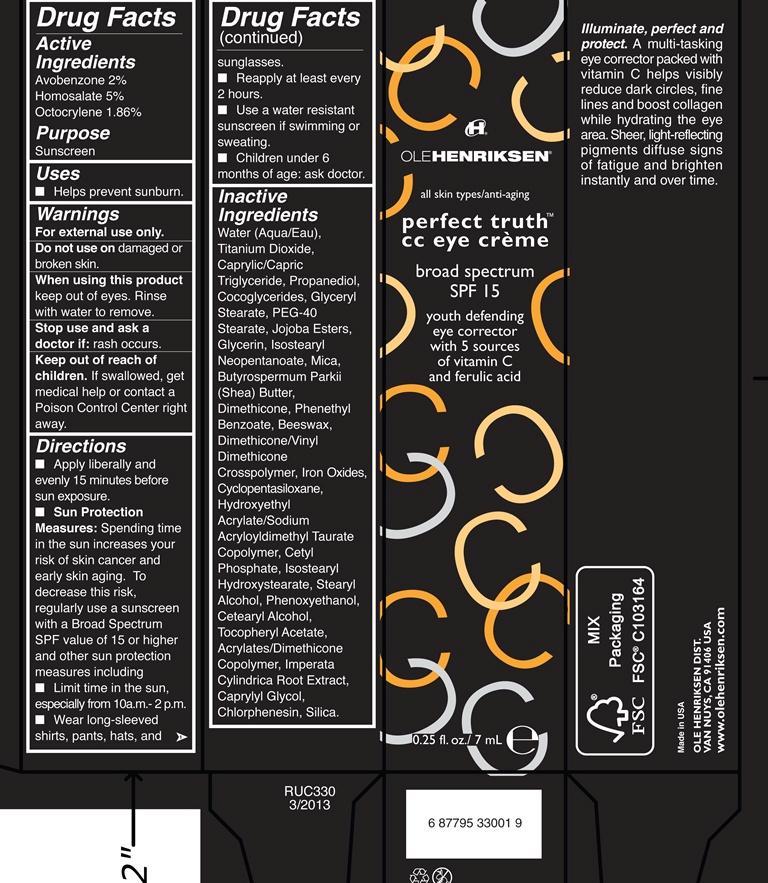 DRUG LABEL: perfect truth cc eye broad spectrum SPF 15
NDC: 51770-110 | Form: CREAM
Manufacturer: Ole Henriksen
Category: otc | Type: HUMAN OTC DRUG LABEL
Date: 20130327

ACTIVE INGREDIENTS: AVOBENZONE 2 g/100 mL; HOMOSALATE 5 g/100 mL; OCTOCRYLENE 1.86 g/100 mL
INACTIVE INGREDIENTS: WATER; TITANIUM DIOXIDE; MEDIUM-CHAIN TRIGLYCERIDES; PROPANEDIOL; COCO-GLYCERIDES; GLYCERYL MONOSTEARATE; PEG-40 STEARATE; GLYCERIN; ISOSTEARYL NEOPENTANOATE; MICA; SHEA BUTTER; DIMETHICONE; PHENETHYL BENZOATE; YELLOW WAX; FERRIC OXIDE RED; FERRIC OXIDE YELLOW; FERROSOFERRIC OXIDE; CYCLOMETHICONE 5; HYDROXYETHYL ACRYLATE/SODIUM ACRYLOYLDIMETHYL TAURATE COPOLYMER (45000 MPA.S AT 1%); CETYL PHOSPHATE; ISOSTEARYL HYDROXYSTEARATE; STEARYL ALCOHOL; PHENOXYETHANOL; CETOSTEARYL ALCOHOL; .ALPHA.-TOCOPHEROL ACETATE; IMPERATA CYLINDRICA ROOT; CAPRYLYL GLYCOL; CHLORPHENESIN; SILICON DIOXIDE

Perfect Truth Eye Cream broad spectrum SPF 15

Active Ingredients Purpose

Avobenzone 2% Sunscreen

Homosalate 5% Sunscreen

Octocrylene 1.86% Sunscreen

Uses
helps prevent sunburn

Keep out of reach of children. If product is swallowed, get medical help or
contact a Poison Control Center right away.

Stop use and ask a doctor if rash occurs

Warnings

For external use only
Do not use on damaged or broken skin
When using this product keep out of eyes. Rinse with water to remove.
Stop use and ask a doctor if rash occurs
Keep out of reach of children. If product is swallowed, get medical help or
contact a Poison Control Center right away.

Directions

Apply liberally 15 minutes before sun exposure
Sun Protection Measures. Spending time in the sun increases your risk of skin
cancer and early skin aging. To decrease this risk, regularly use a sunscreen
with broad spectrum SPF of 15 or higher and other sun protection measures
including:
limit time in the sun, especially from 10 a.m. - 2 p.m.
wear long-sleeve shirts, pants, hats, and sunglasses
Reapply at least every 2 hours
Use a water resistant sunscreen if swimming or sweating
Children under 6 months: Ask a doctor

INACTIVE INGREDIENT

Water (Aqua/Eau), Titanium Dioxide, Caprylic/Capric Triglyceride, Propanediol, Cocoglycerides, Glyceryl Stearate, PEG-40 Stearate, Jojoba Esters, Glycerin, Isostearyl, Neopentanoate, Mica, Butyrospermum Parkii (Shea) Butter, Dimethicone, Phenethyl Benzoate, Beeswax, Dimethicone/Vinyl Dimethicone Crosspolymer, Iron Oxides, Cyclopentasiloxane, Hydroxyethyl Acrylate/Sodium Acryloyldimethyl Taurate Copolymer, Cetyl Phosphate, Isostearyl Hydroxystearate, Stearyl Alcohol, Phenoxyethanol, Cetearyl Alcohol, Tocopheryl Acetate, Acrylates/Dimethicone Copolymer, Imperata Cylindrica Root Extract, Caprylyl Glycol, Chlorphenesin, Silica.

PACKAGE LABEL

Ole Henriksen

all skin types/anti-aging

perfect truth cc eye cream

broad spectrum SPF 15

youth defending eye corrector with 5 sources of vitamin C and ferulic acid

0.25 fl. oz./7 mL